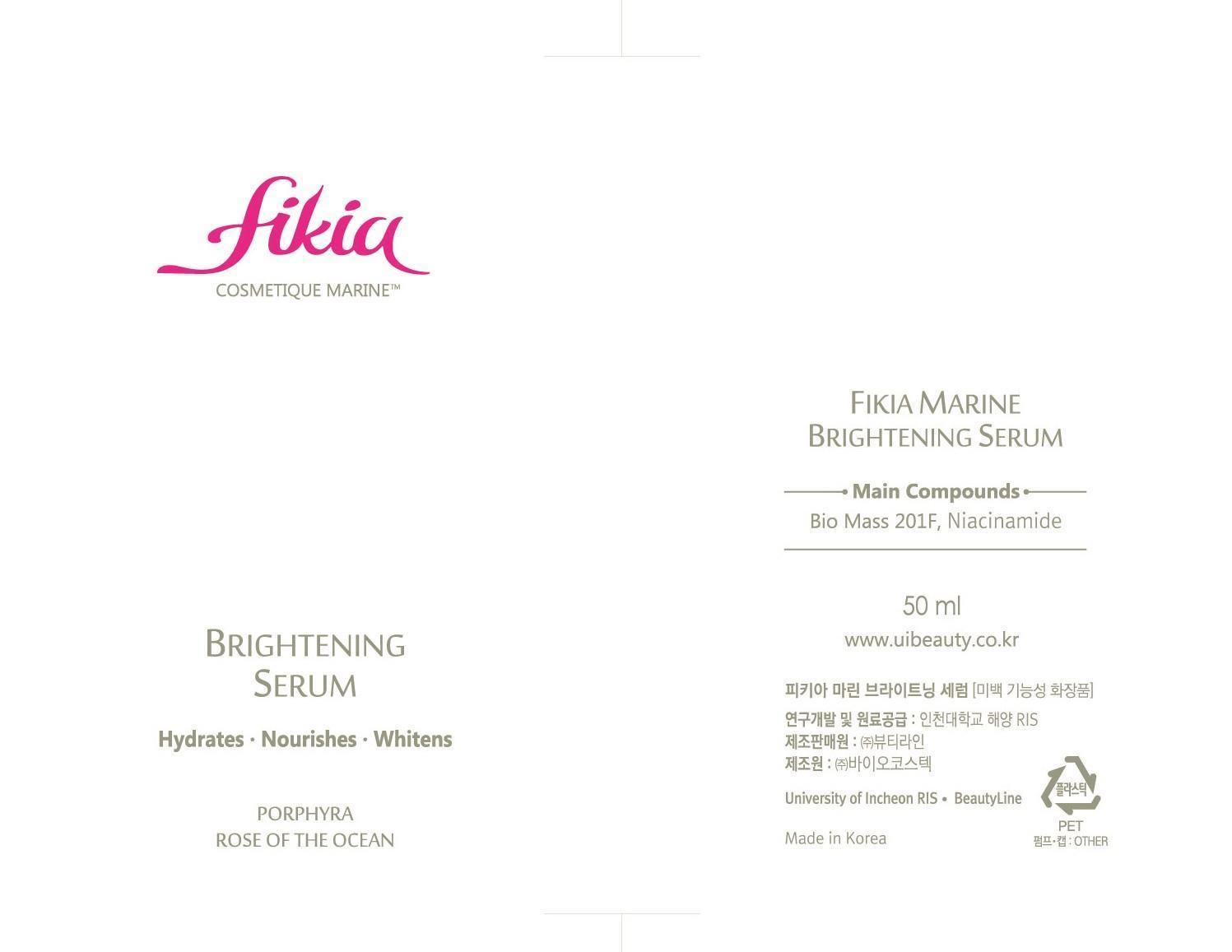 DRUG LABEL: Fikia Marine Brightening Serum
NDC: 69327-1001 | Form: LIQUID
Manufacturer: Beauty Line Co., Ltd.
Category: otc | Type: HUMAN OTC DRUG LABEL
Date: 20141025

ACTIVE INGREDIENTS: GLYCERIN 2 g/100 mL
INACTIVE INGREDIENTS: SODIUM LAURETH SULFATE; BUTYLENE GLYCOL; NIACINAMIDE

Drug Facts

ACTIVE INGREDIENT

glycerin

INACTIVE INGREDIENT

bio mass 201f, niacinamide, water, porphyra tenera ext, sodium hyaluronate, butylene glycol, dipropylene glycol, etc

PURPOSE

whitening
skin protectant

keep out or reach of the children

INDICATIONS AND USAGE

Directions for Use : Apply a moderate amount evenly after Soothing Mist has been fully absorbed.

WARNINGS

1)If in contact with the eyes, wash out thoroughty with water If the symptoms are servere, seek medical advice immediately
2)This product is for exeternal use only. Do not use for internal use
4.Storage and handling precautions
1)If possible, avoid direct sunlight and store in cool and area of low humidity
2)In order to maintain the quality of the product and avoid misuse
3)Avoid placing the product near fire and store out in reach of children

DOSAGE AND ADMINISTRATION

for external use only